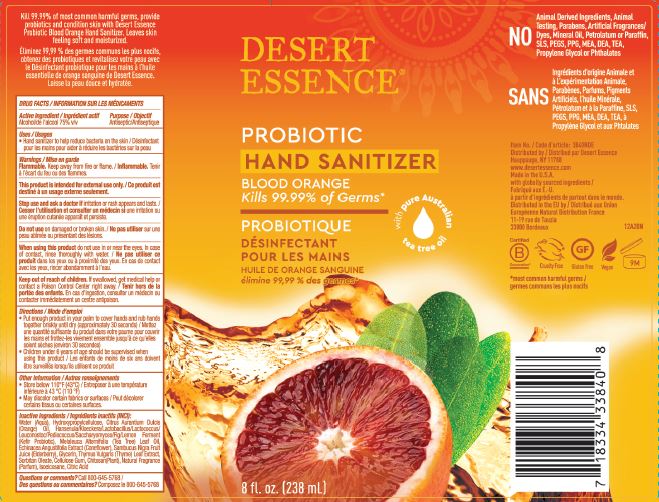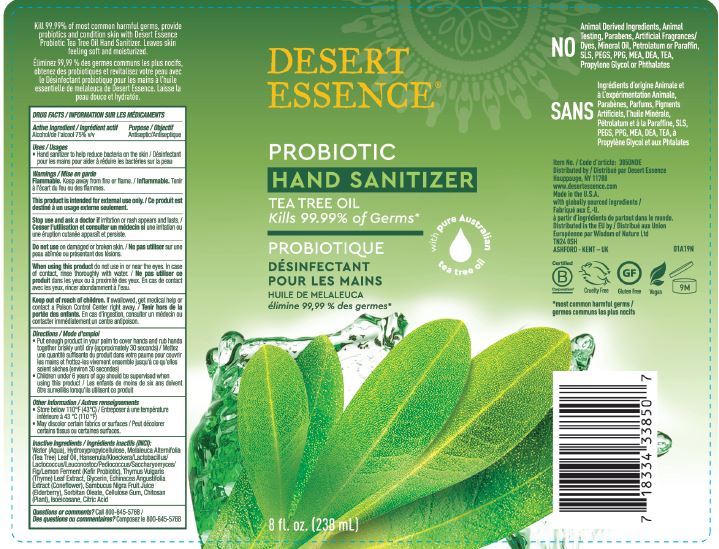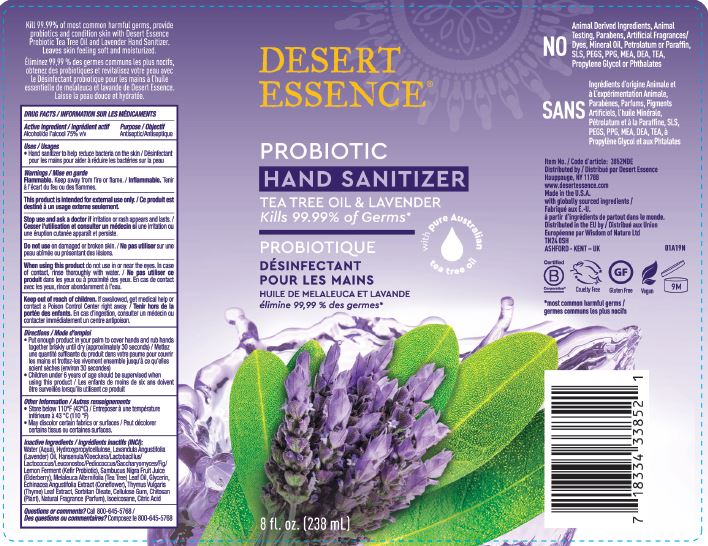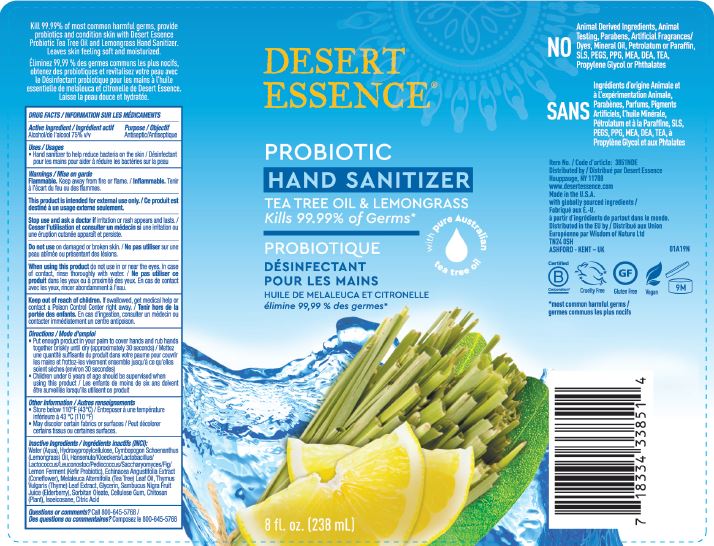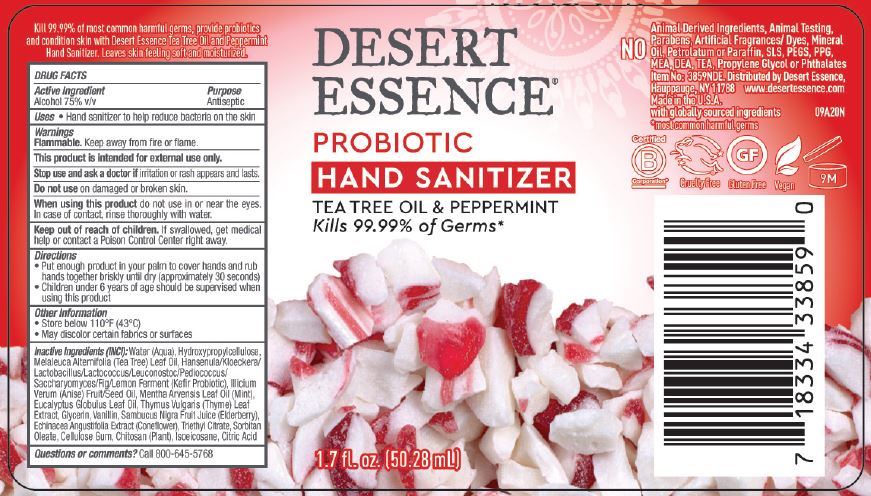 DRUG LABEL: PROBIOTIC HAND SANITIZER
NDC: 81001-101 | Form: GEL
Manufacturer: Country Life Vitamins
Category: otc | Type: HUMAN OTC DRUG LABEL
Date: 20210305

ACTIVE INGREDIENTS: ALCOHOL 75 mL/100 mL
INACTIVE INGREDIENTS: WATER; HYDROXYPROPYL CELLULOSE, UNSPECIFIED; TEA TREE OIL; KEFIRAN; THYME; GLYCERIN; ECHINACEA ANGUSTIFOLIA; EUROPEAN ELDERBERRY JUICE; SORBITAN MONOOLEATE; CARBOXYMETHYLCELLULOSE SODIUM, UNSPECIFIED; CHITOSAN LOW MOLECULAR WEIGHT (20-200 MPA.S); ISOEICOSANE; ANHYDROUS CITRIC ACID; CYMBOPOGON SCHOENANTHUS OIL; LAVENDER OIL; ANISE OIL; MENTHA ARVENSIS LEAF OIL; EUCALYPTUS OIL; VANILLIN; TRIETHYL CITRATE; BASIL OIL; BERGAMOT OIL; CANANGA ODORATA FLOWER; CITRONELLA OIL; GERANIUM OIL, ALGERIAN TYPE; GRAPEFRUIT OIL; LITSEA OIL; ORANGE OIL; SPEARMINT OIL; TANGERINE

DESERT ESSENCE PROBIOTIC HAND SANITIZER (Variants: Tea Tree Oil, Tea Tree & Lavender, Tea Tree & Lemongrass, Tea Tree & Peppermint, Blood Orange)

ACTIVE INGREDIENT

ETHYL ALCOHOL 75% (V/V)

PURPOSE

ANTISEPTIC

USES

- HAND SANITIZER TO HELP REDUCE BACTERIA ON THE SKIN.

WARNINGS

FLAMMABLE. KEEP AWAY FROM FIRE OR FLAME.

THIS PRODUCT IS INTENDED FOR EXTERNAL USE ONLY.

STOP USE AND ASK A DOCTOR IF IRRITATION OR RASH APPEARS AND LASTS.

DO NOT USE ON DAMAGED OR BROKEN SKIN.

WHEN USING THIS PRODUCT DO NOT USE IN OR NEAR THE EYES. IN CASE OF CONTACT, RINSE THOROUGHLY WITH WATER.

KEEP OUT OF REACH OF CHILDREN. IF SWALOWED, GET MEDICAL HELP OR CONTACT A POISON CONTROL CENTER RIGHT AWAY.

DIRECTIONS

- PUT ENOUGH PRODUCT IN YOUR PALM TO COVER HANDS AND RUB HANDS TOGETHER BRISKLY UNTIL DRY (APPROXIMATELY 30 SECONDS).
- CHILDREN UNDER 6 YEARS OF AGE SHOULD BE SUPERVISED WHEN USING THIS PRODUCT.

OTHER INFORMATION

- STORE BELOW 110°F (43°C)
- MAY DISCOLOR CERTAIN FABRICS

INACTIVE INGREDIENTS

TEA TREE & LEMONGRASS: WATER (AQUA), HYDROXYPROPYLCELLULOSE, CYMBOPOGON SCHOENANTHUS (LEMONGRASS) OIL, HANSENULA/KLOECKERA/LACTOBACILLUS/LACTOCOCCUS/LEUCONOSTOC/PEDIOCOCCUS/SACCHARYOMYCES/FIG/LEMON FERMENT (KEFIR PROBIOTIC), ECHINACEA ANGUSTIFOLIA EXTRACT (CONEFLOWER), MELALEUCA ALTERNIFOLIA (TEA TREE) LEAF OIL, THYMUS VULGARIS (THYME) LEAF EXTRACT, GLYCERIN, SAMBUCUS NIGRA FRUIT JUICE (ELDERBERRY), SORBITAN OLEATE, CELLULOSE GUM, CHITOSAN (PLANT), ISOEICOSANE, CITRIC ACID

TEA TREE OIL: WATER (AQUA), HYDROXYPROPYLCELLULOSE, MELALEUCA ALTERNIFOLIA (TEA TREE) LEAF OIL, HANSENULA/KLOECKERA/LACTOBACILLUS/LACTOCOCCUS/LEUCONOSTOC/PEDIOCOCCUS/SACCHARYOMYCES/FIG/LEMON FERMENT (KEFIR PROBIOTIC), THYMUS VULGARIS (THYME) LEAF EXTRACT, GLYCERIN, ECHINACEA ANGUSTIFOLIA EXTRACT (CONEFLOWER), SAMBUCUS NIGRA FRUIT JUICE (ELDERBERRY), SORBITAN OLEATE, CELLULOSE GUM, CHITOSAN (PLANT), ISOEICOSANE, CITRIC ACID

TEA TREE & LAVENDER: WATER (AQUA), HYDROXYPROPYLCELLULOSE, LAVANDULA ANGUSTIFOLIA (LAVENDER) OIL, HANSENULA/KLOECKERA/LACTOBACILLUS/LACTOCOCCUS/LEUCONOSTOC/PEDIOCOCCUS/SACCHARYOMYCES/FIG/LEMON FERMENT (KEFIR PROBIOTIC), SAMBUCUS NIGRA FRUIT JUICE (ELDERBERRY), MELALEUCA ALTERNIFOLIA (TEA TREE) LEAF OIL, GLYCERIN, ECHINACEA ANGUSTIFOLIA EXTRACT (CONEFLOWER), THYMUS VULGARIS (THYME) LEAF EXTRACT, SORBITAN OLEATE, CELLULOSE GUM, CHITOSAN (PLANT), NATURAL FRAGRANCE (PARFUM), ISOEICOSANE, CITRIC ACID

TEA TREE & PEPPERMINT: WATER (AQUA), HYDROXYPROPYLCELLULOSE, MELALEUCA ALTERNIFOLIA (TEA TREE) LEAF OIL, HANSENULA/KLOECKERA/LACTOBACILLUS/LACTOCOCCUS/LEUCONOSTOC/PEDIOCOCCUS/SACCHARYOMYCES/FIG/LEMON FERMENT (KEFIR PROBIOTIC), ILLICIUM VERUM (ANISE) FRUIT/SEED OIL, MENTHA ARVENSE LEAF OIL (MINT), EUCALYPTUS GLOBULUS LEAF OIL, THYMUS VULGARIS (THYME) LEAF EXTRACT, GLYCERIN, VANILLIN, SAMBUCUS NIGRA FRUIT JUICE (ELDERBERRY), ECHINACEA ANGUSTIFOLIA EXTRACT (CONEFLOWER), TRIETHYL CITRATE, SORBITAN OLEATE, CELLULOSE GUM, CHITOSAN (PLANT), ISOEICOSANE, CITRIC ACID

BLOD ORANGE: Illicium Verum (Anise) Fruit/Seed Oil, Ocimum Basilicum (Basil) Oil, Citrus Aurantium Bergamia Fruit Oil (Bergamot), Cananga Odorata Flower Oil (Ylang), Cymbopogon Nardum (Citronella) Oil, Pelargonium Graveolens Oil (Geranium), Citrus Paradisi (Grapefruit) Peel Oil, Litsea Cubeba Fruit Oil, Citrus Aurantium Dulcis (Orange) Oil, Mentha Viridis (Spearmint) Leaf Oil, Citrus Reticulata (Tangerine) Peel Oil